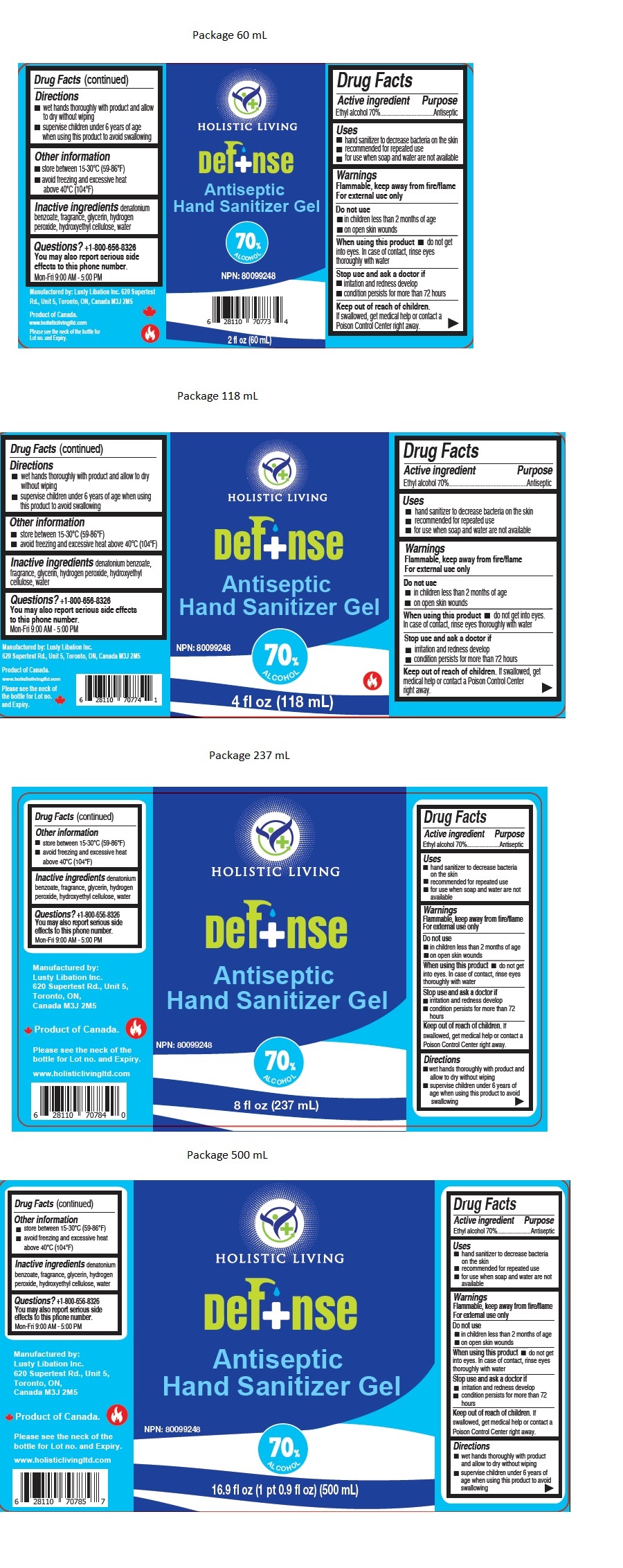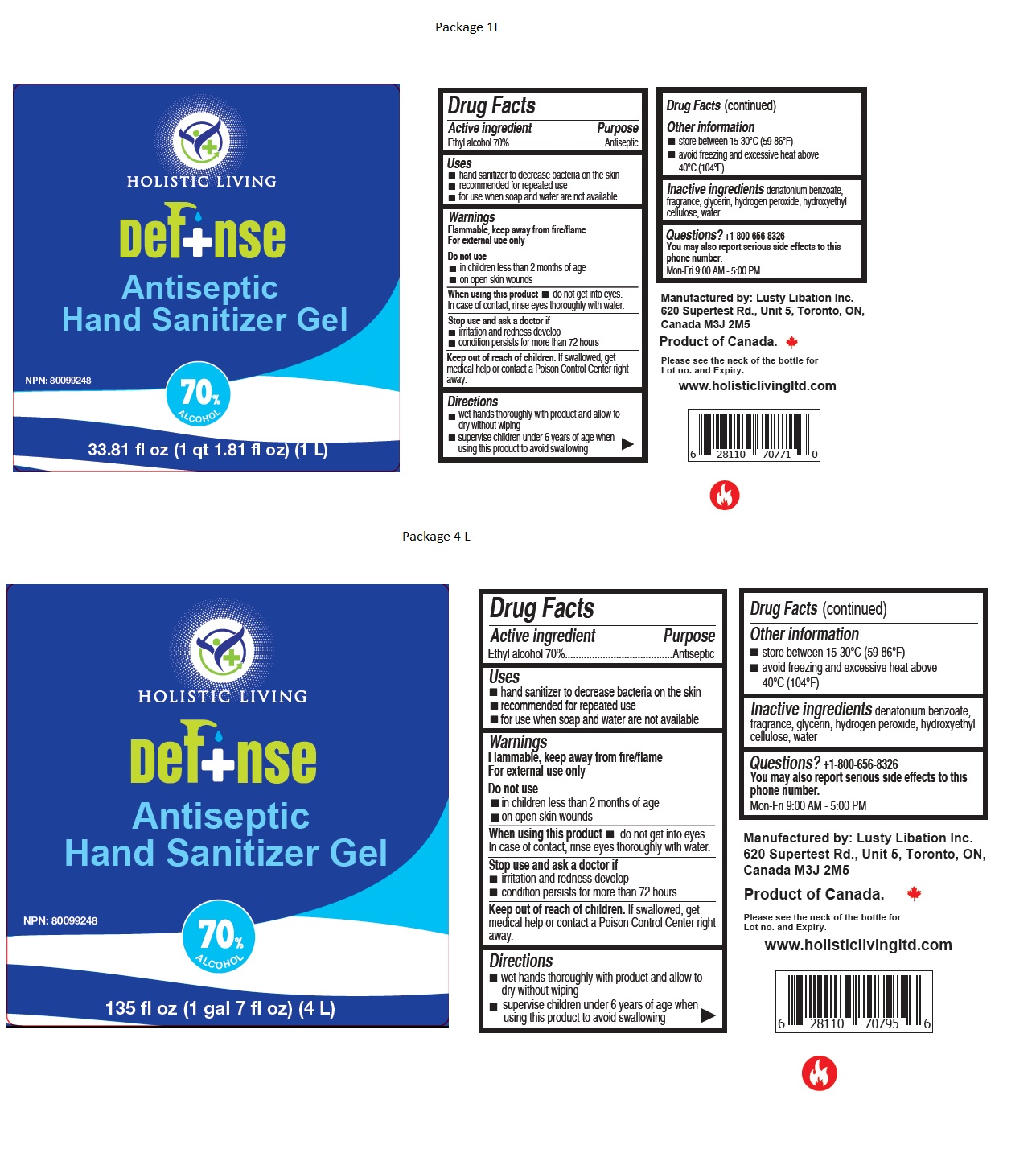 DRUG LABEL: Defnse Antiseptic Hand Sanitizer
NDC: 77846-888 | Form: GEL
Manufacturer: Lusty Libation Ltd.
Category: otc | Type: HUMAN OTC DRUG LABEL
Date: 20200728

ACTIVE INGREDIENTS: ALCOHOL 70 mL/100 mL
INACTIVE INGREDIENTS: DENATONIUM BENZOATE; GLYCERIN; HYDROGEN PEROXIDE; HYDROXYETHYL CELLULOSE, UNSPECIFIED; WATER

Def+nse Antiseptic Hand Sanitizer Gel

Active ingredient

Ethyl alcohol 70%

Purpose

Antiseptic

Uses

- hand sanitizer to decrease bacteria on the skin
- recommended for repeated use
- for use when soap and water are not available

Warnings

Flammable, keep away from fire/flame
For external use only

Do not use

- in children less than 2 months of age
- on open skin wounds

When using this product • do not get into eyes. In case of contact, rinse eyes thoroughly with water

Stop use and ask a doctor if

- irritation and redness develop
- condition persists for more than 72 hours

Keep out of reach of children. If swallowed, get medical help or contact a Poison Control Center right away.

Directions

- wet hands thoroughly with product and allow to dry without wiping
- supervise children under 6 years of age when using this product to avoid swallowing

Other information

- store between 15-30°C (59-86°F)
- avoid freezing and excessive heat above 40°C (104°F)

Inactive ingredients

denatonium benzoate, fragrance, glycerin, hydrogen peroxide, hydroxyethyl cellulose, water

Questions?

You may also report serious side effects to this phone number.
Mon-Fri 9:00 AM - 5:00 PM

HOLISTIC LIVING

NPN: 80099248

Manufactured by: Lusty Libation Inc. 620 Supertest Rd., Unit 5, Toronto, ON, Canada M3J 2M5

Product of Canada.

www.holisticlivingltd.com